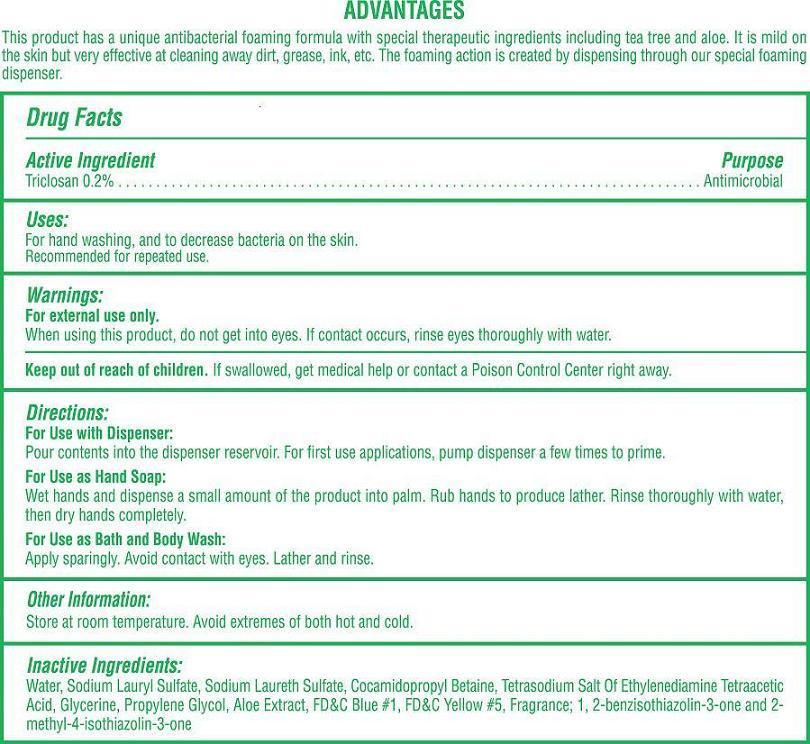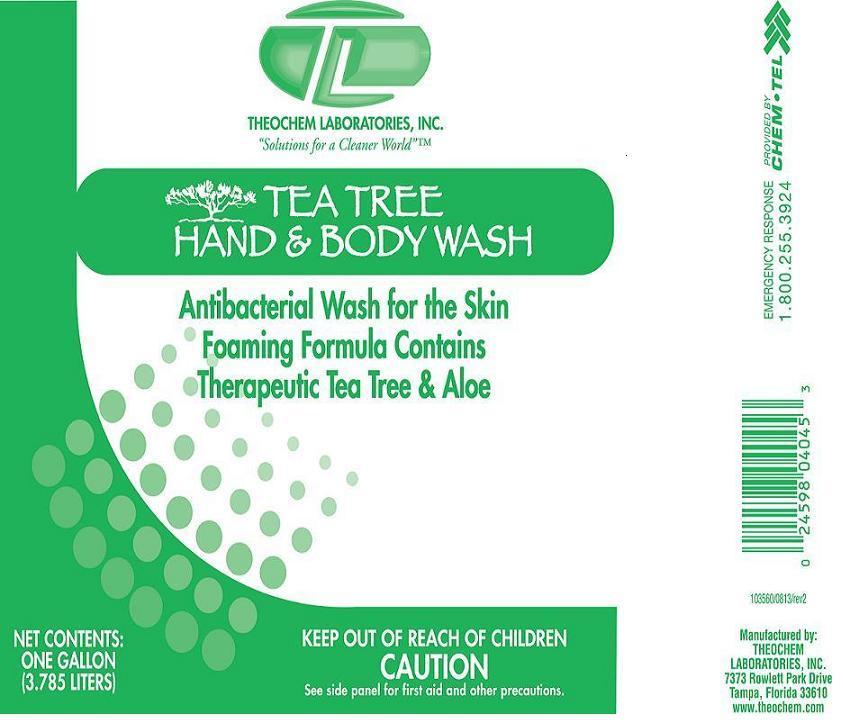 DRUG LABEL: Theochem Tea Tree Hand and Body Wash
NDC: 68878-120 | Form: SOAP
Manufacturer: Theochem Laboratories
Category: otc | Type: HUMAN OTC DRUG LABEL
Date: 20131003

ACTIVE INGREDIENTS: TRICLOSAN 2 g/1 L
INACTIVE INGREDIENTS: WATER

Tea Tree Hand and Body Wash

Active Ingredient

Triclosan 0.2%

Purpose:

Antimicrobial

Uses:

For Hand Washing, and to decrease bacteria on the skin.

Recommended for repeated use.

Warnings:

For external use only.

When using this product, do not get into eyes. If contact occurs, rinse eyes thoroughly with water

Keep out of reach of children

If swallowed, get medical help or contact a Poison Control Center right away.

Directions:

For use with Dispenser:

Pour contents into the dispenser reservoir. For first use applications, pump dispenser a few times to prime.

For use as Hand Soap:

Wet hands and dispense a small amount of the product into palm. Rub hands to produce lather. Rinse thoroughly with water, then dry hands completely.

For use as Bath and Body Wash:

Apply sparingly. Avoid contact with eyes. Lather and rinse.

Other Information

Store at room temperature. Avoid extremes of both hot and cold.

Inactive Ingredients:

Water, Sodium Lauryl Sulfate, Sodium Laureth Sulfate, Cocamidopropyl Betaine, Tetrasodium Salt of Ethylenediamine Tetraacetic Acid, Glycerine, Propylene Glycol, Aloe Extract, FD&C Blue # 1, FD&C Yellow # 5, Fragrance, 1,2-benzisothiazolin-3-one and 2-methyl-4-isothiazolin-3-one.

PRINCIPAL DISPLAY PANEL

TEA TREE HAND & BODY WASH

NET CONTENTS: ONE GALLON (3.785 LITERS)